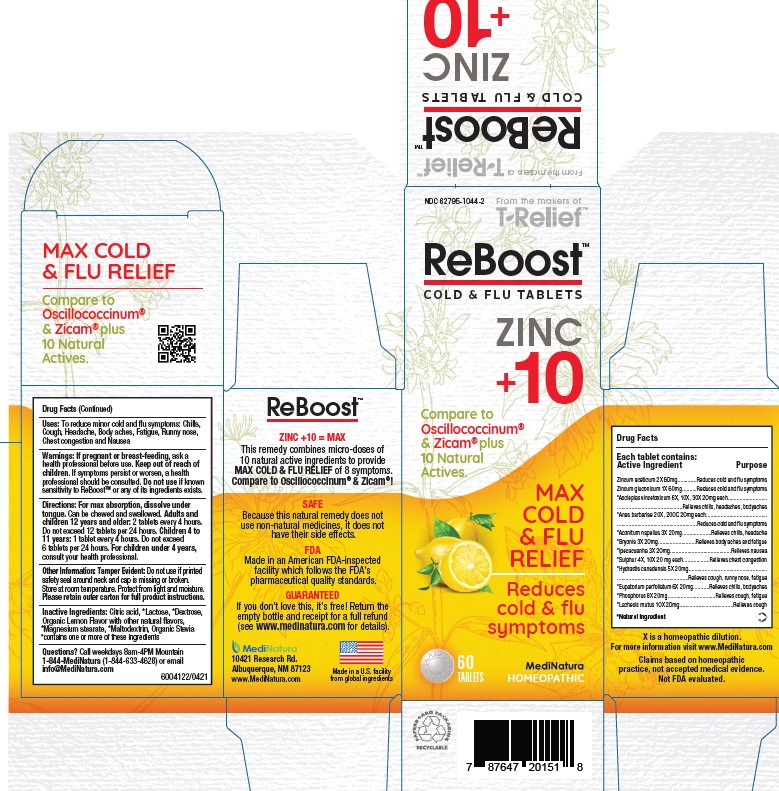 DRUG LABEL: Reboost
NDC: 62795-1044 | Form: TABLET
Manufacturer: MediNatura Inc.
Category: homeopathic | Type: HUMAN OTC DRUG LABEL
Date: 20230605

ACTIVE INGREDIENTS: ACONITUM NAPELLUS 3 [hp_X]/1 1; BRYONIA ALBA ROOT 3 [hp_X]/1 1; EUPATORIUM PERFOLIATUM FLOWERING TOP 6 [hp_X]/1 1; LACHESIS MUTA VENOM 10 [hp_X]/1 1; GOLDENSEAL 5 [hp_X]/1 1; PHOSPHORUS 8 [hp_X]/1 1; VINCETOXICUM HIRUNDINARIA ROOT 6 [hp_X]/1 1; ZINC GLUCONATE 1 [hp_X]/1 1; ZINC ACETATE ANHYDROUS 2 [hp_X]/1 1; CAIRINA MOSCHATA HEART/LIVER AUTOLYSATE 20 [hp_X]/1 1; IPECAC 3 [hp_X]/1 1; SULFUR 4 [hp_X]/1 1
INACTIVE INGREDIENTS: LACTOSE, UNSPECIFIED FORM; MAGNESIUM STEARATE; CITRIC ACID MONOHYDRATE; STEVIA REBAUDIUNA LEAF; MALTODEXTRIN; DEXTROSE

Reboost

KEEP OUT OF REACH OF CHILDREN

Uses:

To reduce minor cold and flu symptoms: Chills,
Cough, Headache, Body aches, Fatigue, Runny nose,
Chest congestion and Nausea

Warnings:

If pregnant or breast-feeding, ask a
health professional before use. Keep out of reach of
children. If symptoms persist or worsen, a health
professional should be consulted. Do not use if known
sensitivity to ReBoostTM or any of its ingredients exists.

Directions:

For max absorption, dissolve under
tongue. Can be chewed and swallowed. Adults and
children 12 years and older: 2 tablets every 4 hours.
Do not exceed 12 tablets per 24 hours. Children 4 to
11 years: 1 tablet every 4 hours. Do not exceed
6 tablets per 24 hours. For children under 4 years,
consult your health professional.

Active Ingredient

Each tablet contains:
Active Ingredient Purpose
Zincum aceticum 2X 60mg.............Reduces cold and flu symptoms
Zincum gluconicum 1X 60mg..........Reduces cold and flu symptoms
*Asclepias vincetoxicum 6X, 10X, 30X 20mg each...........................
.............................................Relieves chills, headaches, bodyaches
*Anas barbariae 20X, 200C 20mg each..........................................
.......................................................Reduces cold and flu symptoms
*Aconitum napellus 3X 20mg....................Relieves chills, headache
*Bryonia 3X 20mg..........................Relieves body aches and fatigue
*Ipecacuanha 3X 20mg..........................................Relieves nausea
*Sulphur 4X, 10X 20 mg each..................Relieves chest congestion
*Hydrastis canadensis 5X 20mg......................................................
.................................................Relieves cough, runny nose, fatigue
*Eupatorium perfoliatum 6X 20mg...........Relieves chills, bodyaches
*Phosphorus 8X 20mg.................................Relieves cough, fatigue
*Lachesis mutus 10X 20mg.....................................Relieves cough
*Natural Ingredient
X is a homeopathic dilution.

Inactive Ingredients:

Citric acid, *Lactose, *Dextrose,
Organic Lemon Flavor with other natural flavors,
*Magnesium stearate, *Maltodextrin, Organic Stevia
*contains one or more of these ingredients

Purpose

Reduces
cold & flu
symptoms